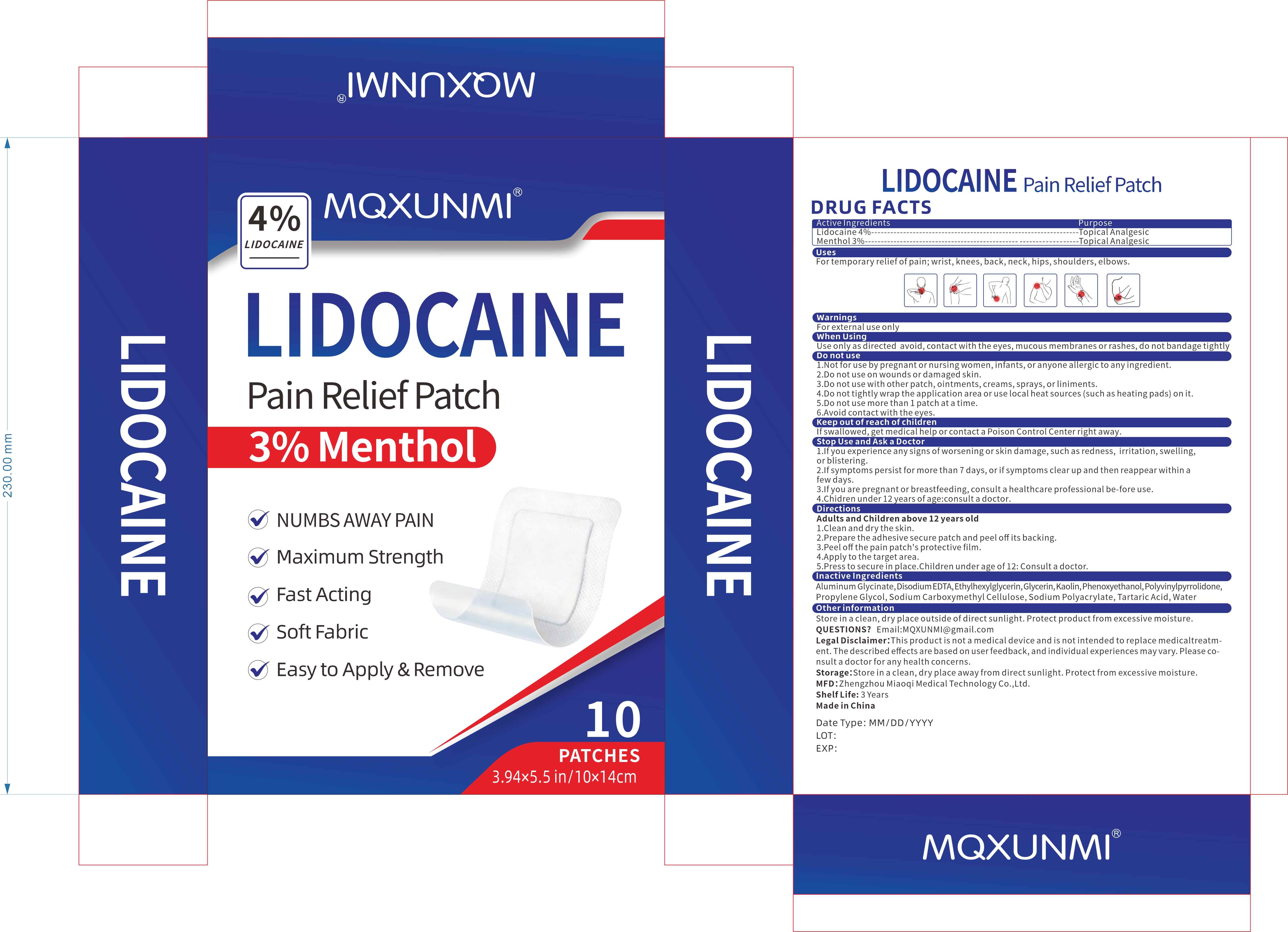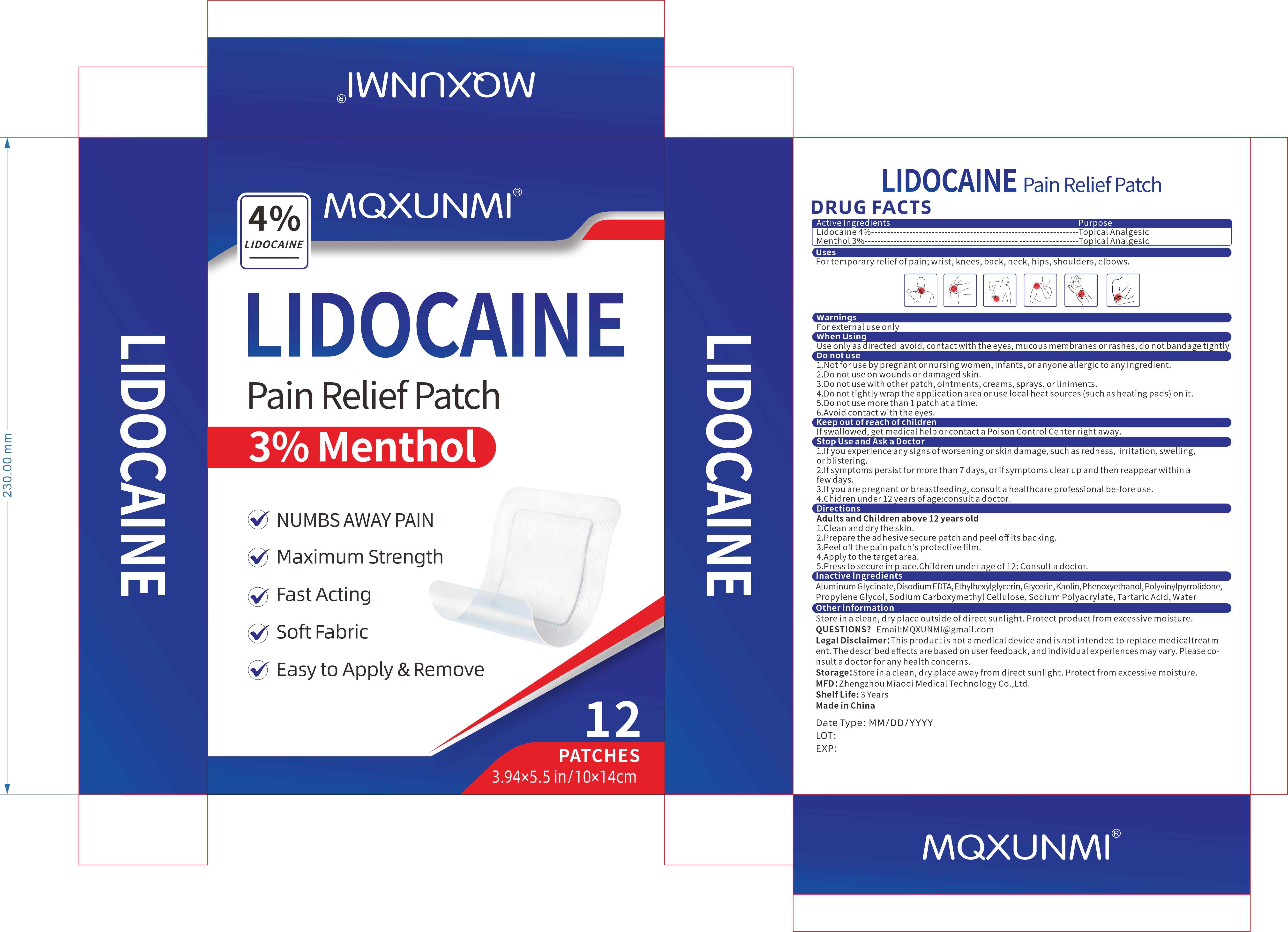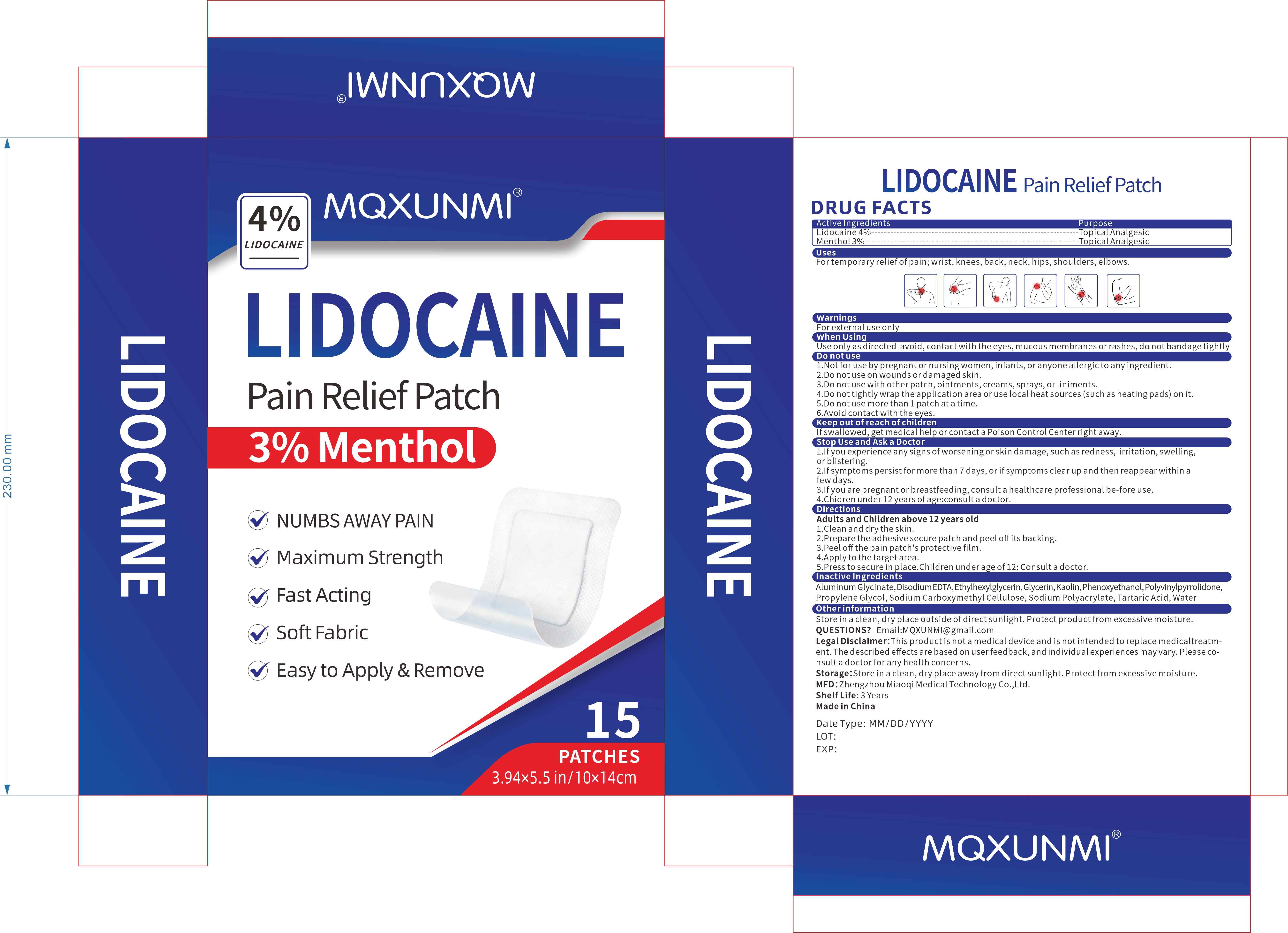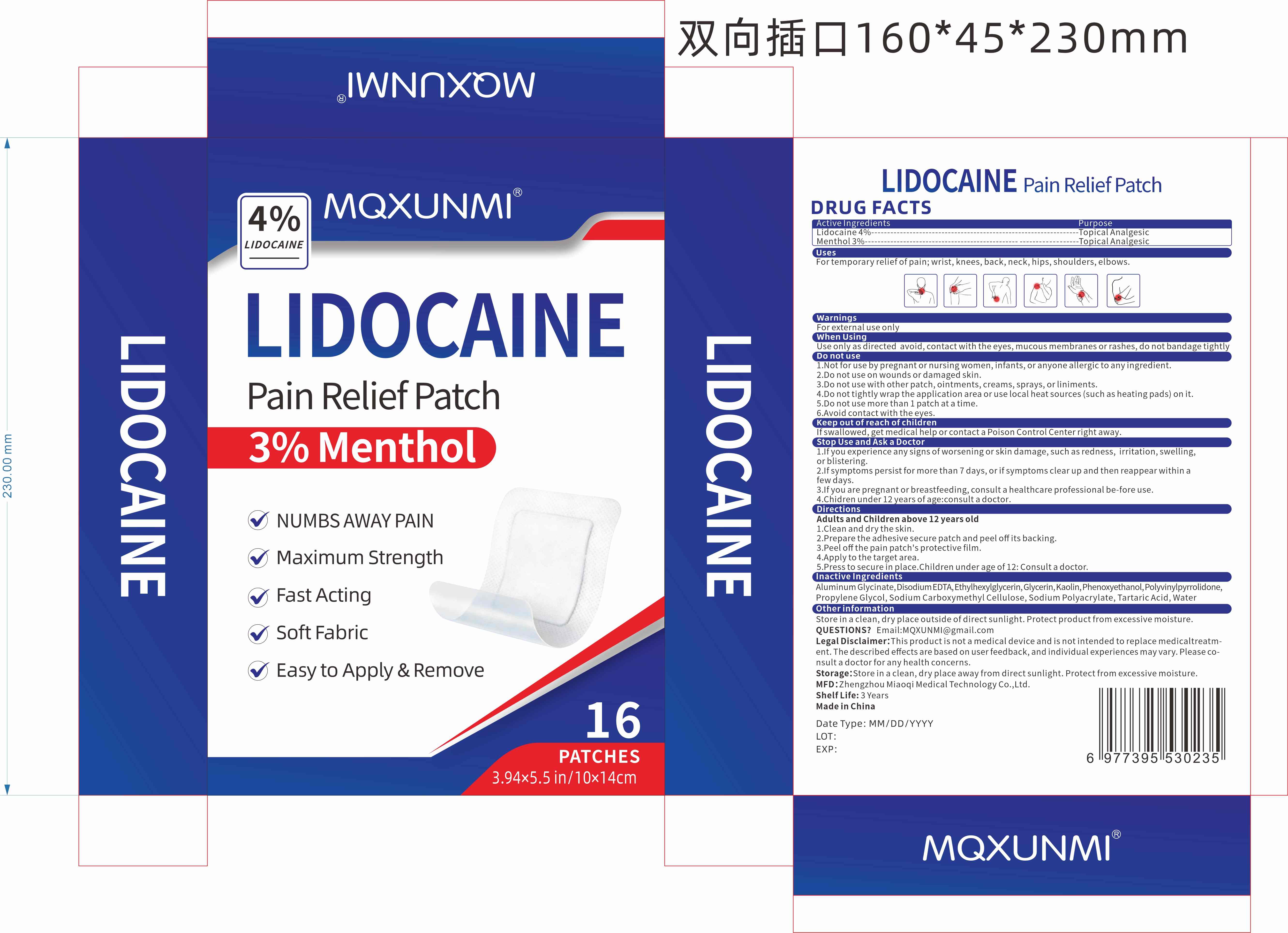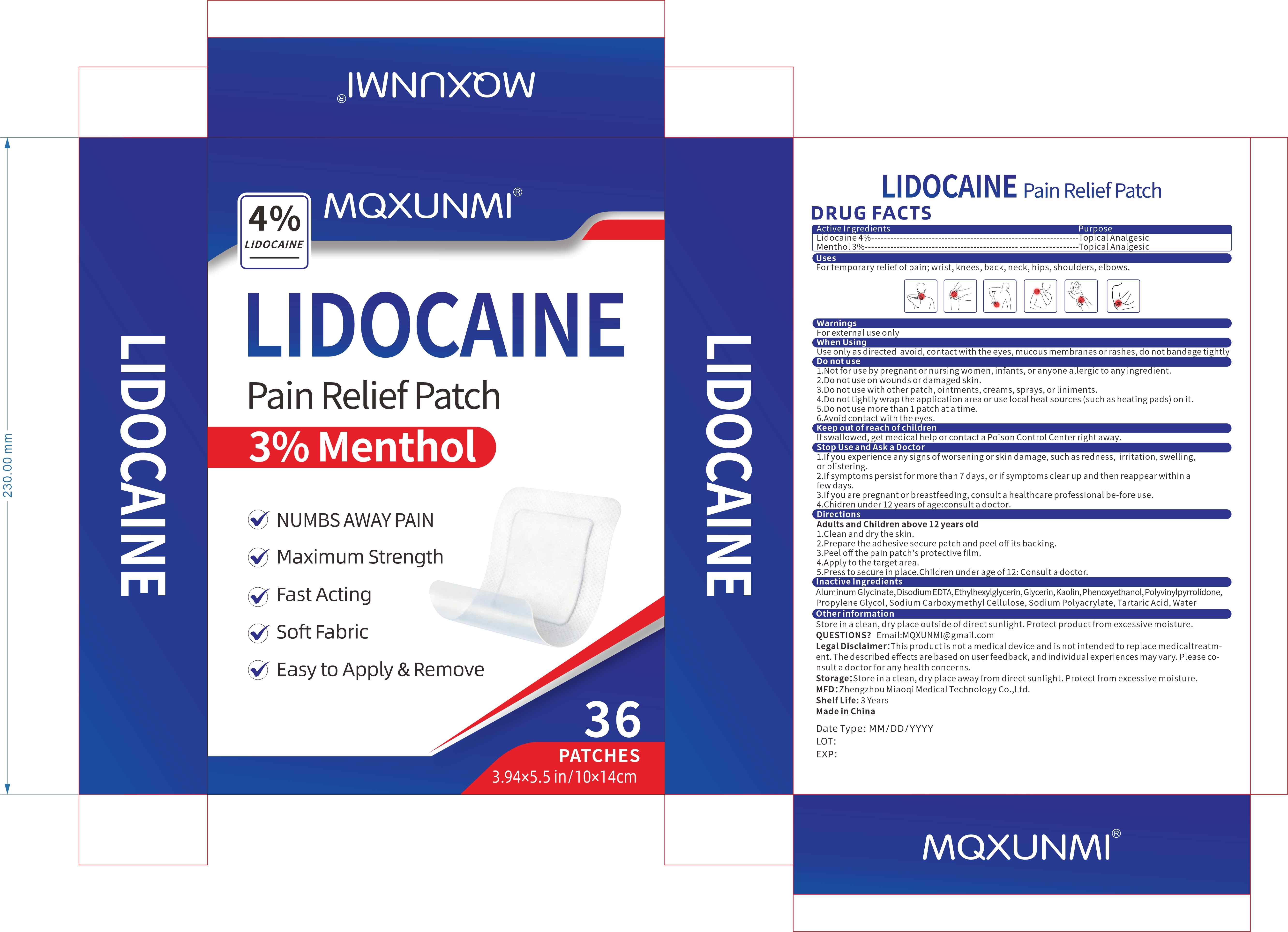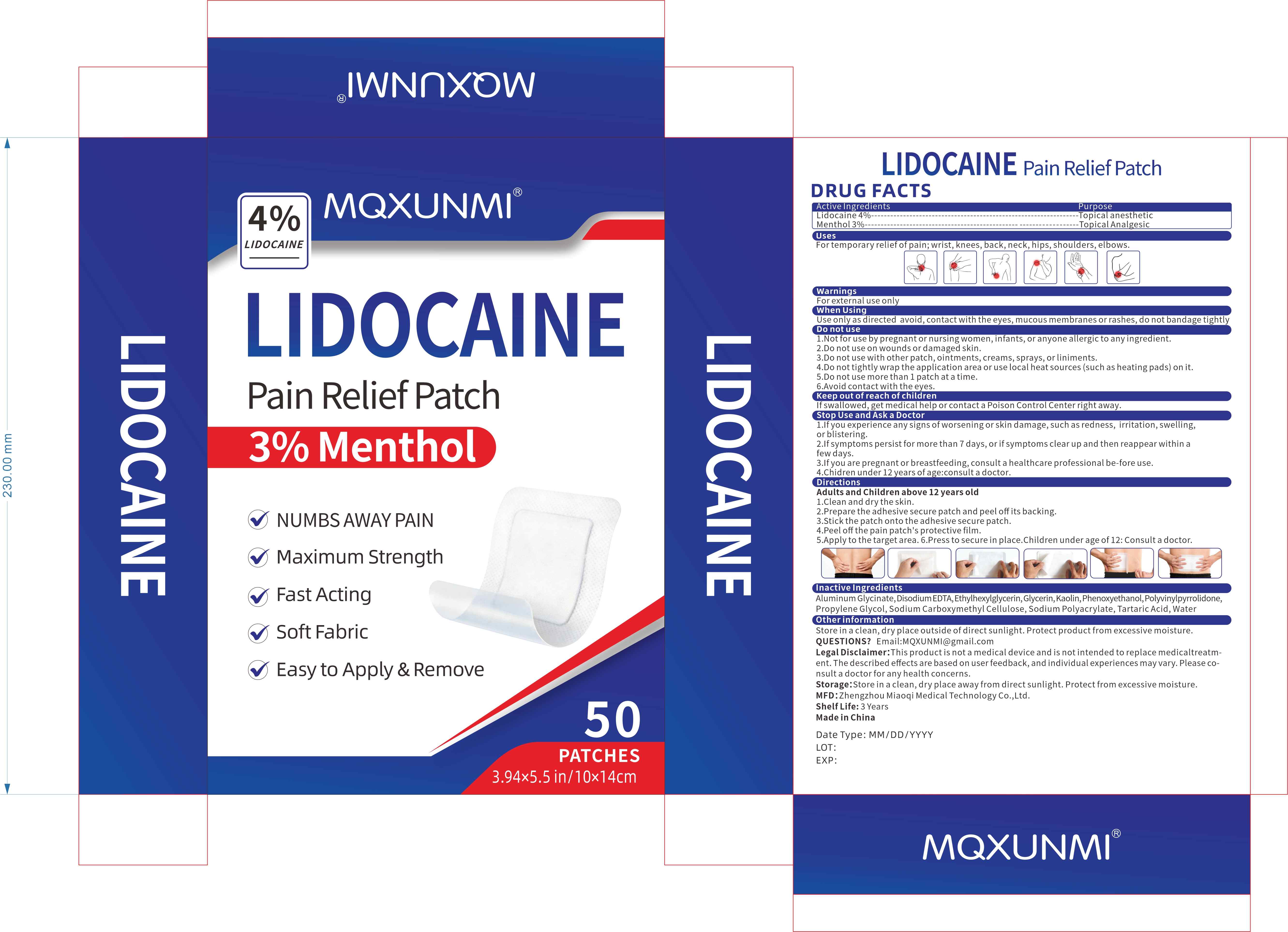 DRUG LABEL: MQXUNMI LIDOCAINE Pain Relief Patch
NDC: 83781-015 | Form: PATCH
Manufacturer: Zhengzhou Miaoqi Medical Technology Co., Ltd.
Category: otc | Type: HUMAN OTC DRUG LABEL
Date: 20260128

ACTIVE INGREDIENTS: MENTHOL 3 g/100 1; LIDOCAINE 4 g/100 1
INACTIVE INGREDIENTS: DIHYDROXYALUMINUM AMINOACETATE; GLYCERIN; POLYACRYLIC ACID (250000 MW); POVIDONE K90; PROPYLENE GLYCOL; SODIUM POLYACRYLATE (2500000 MW); METHYLPARABEN; TITANIUM DIOXIDE; POLYSORBATE 80; TARTARIC ACID; WATER; KAOLIN; EDETATE DISODIUM; PROPYLPARABEN

83781-015

Active Ingredient

Lidocaine 4%
Menthol 3%

Purpose

Topical Analgesic
wrist, knees, back, neck, hips, shoulders, elbows.

Use

For temporary relief of pain

Warnings

For external use only

Do not use

1.Not for use by pregnant or nursing women, infants, or anyone allergic to any ingredient.
2.Do not use on wounds or damaged skin.
3.Do not use with other patch, ointments, creams, sprays, or liniments.
4.Do not tightly wrap the application area or use local heat sources (such as heating pads) on it.
5.Do not use more than 1 patch at a time.
6.Avoid contact with the eyes.
7.Keep out of reach of children. If swallowed, get medical help or contact a Poison Control Center right away

When Using

use only as directed

█ avoid contact with the eyes, mucous membranes or rashes

█ do not bandage tightly

Stop Use

1.If you experience any signs of worsening or skin damage, such as redness, irritation, swelling, or blistering.
2.If symptoms persist for more than 7 days, or if symptoms clear up and then reappear within a few days.
3.If you are pregnant or breastfeeding, consult a healthcare professional before use.
4.Chidren under 12 years of age:consult a doctor.

Ask Doctor

1.If you experience any signs of worsening or skin damage, such as redness, irritation, swelling, or blistering.
2.If symptoms persist for more than 7 days, or if symptoms clear up and then reappear within a few days.
3.If you are pregnant or breastfeeding, consult a healthcare professional before use.
4.Chidren under 12 years of age:consult a doctor.

Keep Out Of Reach Of Children

If swallowed, get medical help or contact a Poison Control Center right away.

Directions

Adults and Children above 12 years old
1.Clean and dry the skin.
2.Prepare the adhesive secure patch and peel off its backing.
3.Peel off the pain patch's protective film.
4.Apply to the target area.
5.Press to secure in place.
Children under age of 12: Consult a doctor.

Other information

Store in a clean, dry place outside of direct sunlight. Protect product from excessive moisture.

Inactive ingredients

Aluminum Glycinate, Disodium EDTA, Ethylhexylglycerin, Glycerin, Kaolin, Phenoxyethanol, Polyvinylpyrrolidone, Propylene Glycol, Sodium Carboxymethyl Cellulose, Sodium Polyacrylate, Tartaric Acid, Water

Questions

Email:MQXUNMI@gmail.com